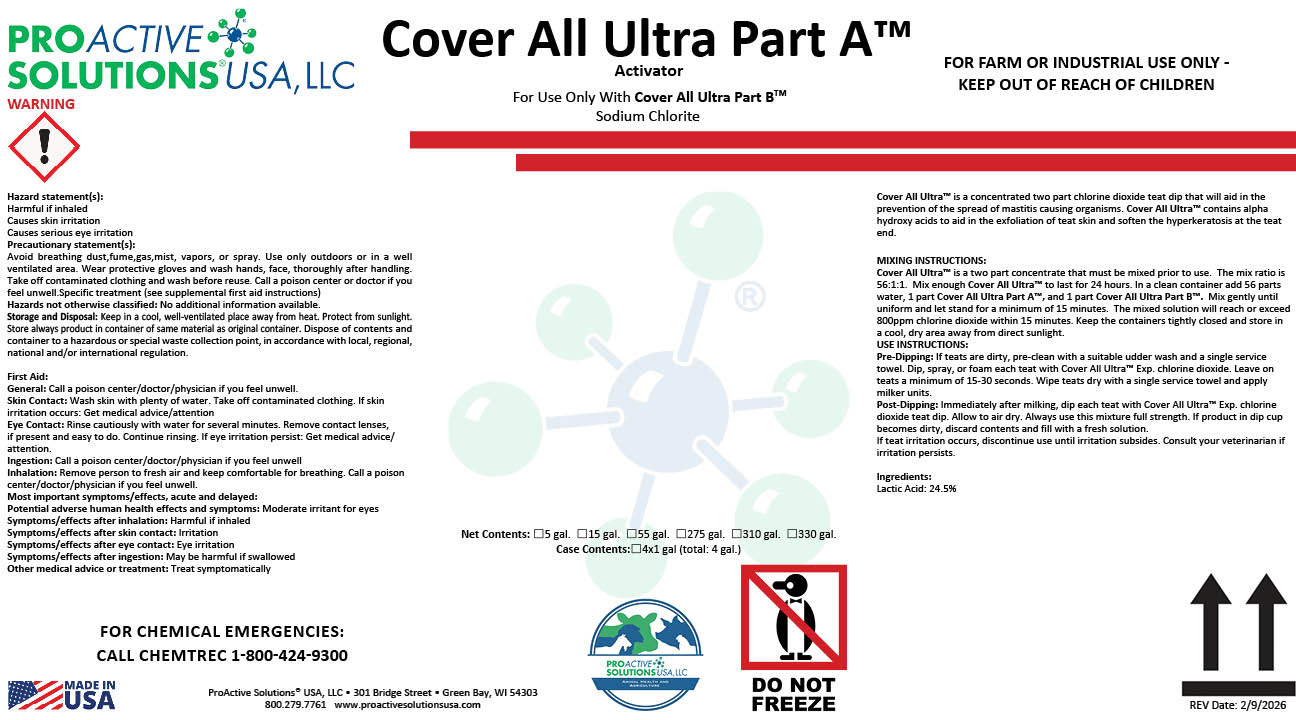 DRUG LABEL: Cover All Ultra Part A
NDC: 63927-4123 | Form: SOLUTION
Manufacturer: ProActive Solutions USA, LLC
Category: animal | Type: OTC ANIMAL DRUG LABEL
Date: 20260210

ACTIVE INGREDIENTS: LACTIC ACID 24.5 kg/100 kg

Cover All Ultra Part A

Cover All Ultra Part A

MIXING INSTRUCTIONS:
Cover All Ultra™ is a two part concentrate that must be mixed prior to use. The mix ratio is
56:1:1. Mix enough Cover All Ultra™ to last for 24 hours. In a clean container add 56 parts
water, 1 part Cover All Ultra Part A™, and 1 part Cover All Ultra Part B™. Mix gently until
uniform and let stand for a minimum of 15 minutes. The mixed solution will reach or exceed
800ppm chlorine dioxide within 15 minutes. Keep the containers tightly closed and store in
a cool, dry area away from direct sunlight.
USE INSTRUCTIONS:
Pre-Dipping: If teats are dirty, pre-clean with a suitable udder wash and a single service
towel. Dip, spray, or foam each teat with Cover All Ultra™ Exp. chlorine dioxide. Leave on
teats a minimum of 15-30 seconds. Wipe teats dry with a single service towel and apply
milker units.
Post-Dipping: Immediately after milking, dip each teat with Cover All Ultra™ Exp. chlorine
dioxide teat dip. Allow to air dry. Always use this mixture full strength. If product in dip cup
becomes dirty, discard contents and fill with a fresh solution.
If teat irritation occurs, discontinue use until irritation subsides. Consult your veterinarian if
irritation persists.
Ingredients:
Lactic Acid: 24.5%

Hazard statement(s):
Harmful if inhaled
Causes skin irritation
Causes serious eye irritation
Precautionary statement(s):
Avoid breathing dust,fume,gas,mist, vapors, or spray. Use only outdoors or in a well
ventilated area. Wear protective gloves and wash hands, face, thoroughly after handling.
Take off contaminated clothing and wash before reuse. Call a poison center or doctor if you
feel unwell.Specific treatment (see supplemental first aid instructions)
Hazards not otherwise classified: No additional information available.
Storage and Disposal: Keep in a cool, well-ventilated place away from heat. Protect from sunlight.
Store always product in container of same material as original container. Dispose of contents and
container to a hazardous or special waste collection point, in accordance with local, regional,
national and/or international regulation.
First Aid:
General: Call a poison center/doctor/physician if you feel unwell.
Skin Contact: Wash skin with plenty of water. Take off contaminated clothing. If skin
irritation occurs: Get medical advice/attention
Eye Contact: Rinse cautiously with water for several minutes. Remove contact lenses,
if present and easy to do. Continue rinsing. If eye irritation persist: Get medical advice/
attention.
Ingestion: Call a poison center/doctor/physician if you feel unwell
Inhalation: Remove person to fresh air and keep comfortable for breathing. Call a poison
center/doctor/physician if you feel unwell.
Most important symptoms/effects, acute and delayed:
Potential adverse human health effects and symptoms: Moderate irritant for eyes
Symptoms/effects after inhalation: Harmful if inhaled
Symptoms/effects after skin contact: Irritation
Symptoms/effects after eye contact: Eye irritation
Symptoms/effects after ingestion: May be harmful if swallowed
Other medical advice or treatment: Treat symptomatically